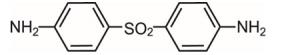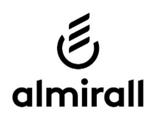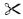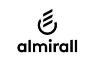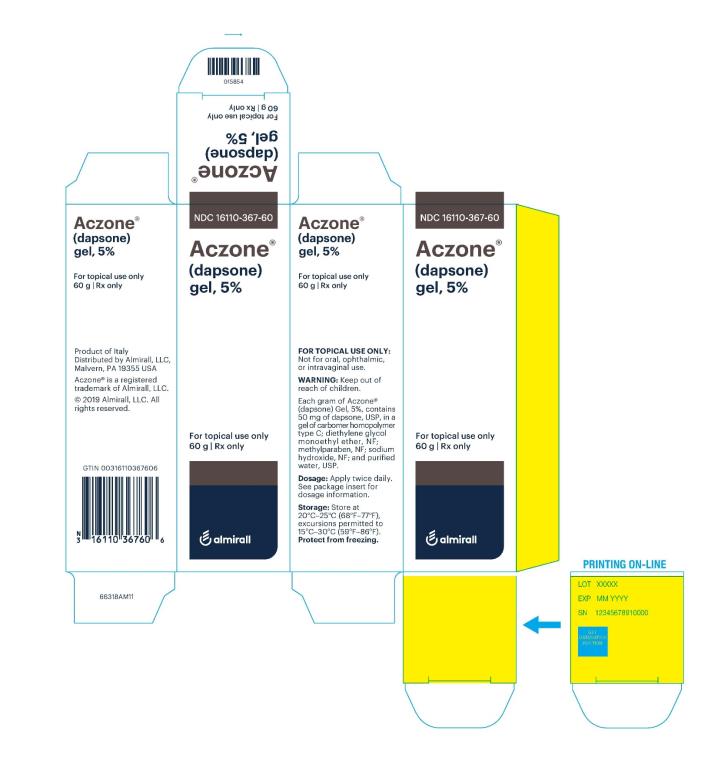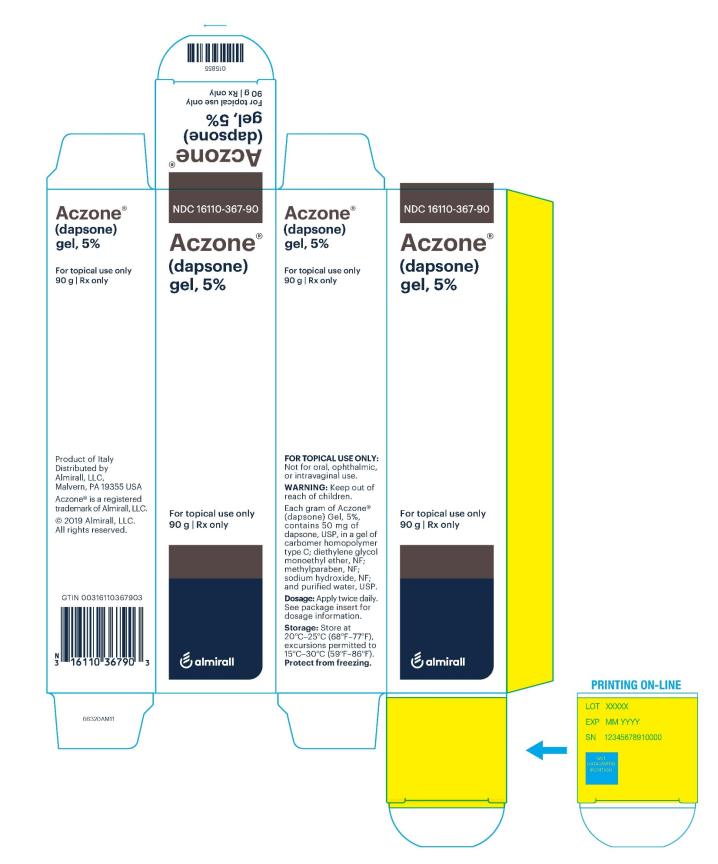 DRUG LABEL: ACZONE
NDC: 16110-367 | Form: GEL
Manufacturer: ALMIRALL, LLC
Category: prescription | Type: HUMAN PRESCRIPTION DRUG LABEL
Date: 20190701

ACTIVE INGREDIENTS: DAPSONE 50 mg/1 g
INACTIVE INGREDIENTS: CARBOMER HOMOPOLYMER TYPE C (ALLYL PENTAERYTHRITOL CROSSLINKED); DIETHYLENE GLYCOL MONOETHYL ETHER; METHYLPARABEN; SODIUM HYDROXIDE; WATER

HIGHLIGHTS OF PRESCRIBING INFORMATION

These highlights do not include all the information needed to use ACZONE® Gel, 5% safely and effectively. See full prescribing information for ACZONE® Gel, 5%.
ACZONE® (dapsone) Gel, 5%, for topical use
Initial U.S. Approval: 1955

1 INDICATIONS AND USAGE

ACZONE® Gel is indicated for the topical treatment of acne vulgaris (1).

2 DOSAGE AND ADMINISTRATION

- Apply twice daily (2).
- Apply approximately a pea-sized amount of ACZONE Gel, 5%, in a thin layer to the acne affected area (2).
- If there is no improvement after 12 weeks, treatment with ACZONE Gel, 5%, should be reassessed (2).
- For topical use only. Not for oral, ophthalmic, or intravaginal use (2).

3 DOSAGE FORMS AND STRENGTHS

Gel, 5% (3).

4 CONTRAINDICATIONS

None (4).

5 WARNINGS AND PRECAUTIONS

- Methemoglobinemia: Cases of methemoglobinemia have been reported. Discontinue ACZONE gel if signs of methemoglobinemia occur (5.1).
- Hematologic Effects: Some subjects with G6PD deficiency using ACZONE Gel developed laboratory changes suggestive of hemolysis. (5.2)(8.6).

6 ADVERSE REACTIONS

Most common adverse reactions (incidence ≥ 10%) are oiliness/peeling, dryness and erythema at the application site (6).

To report SUSPECTED ADVERSE REACTIONS, contact Allergan at 1-800-678-1605 or FDA at 1-800-FDA-1088 or www.fda.gov/medwatch.

7 DRUG INTERACTIONS

- Trimethoprim/sulfamethoxazole (TMP/SMX) increases the level of dapsone and its metabolites (7.1).
- Topical benzoyl peroxide used at the same time as ACZONE may result in temporary local yellow or orange skin discoloration (7.2).

FULL PRESCRIBING INFORMATION

1 INDICATIONS AND USAGE

ACZONE® Gel, 5%, is indicated for the topical treatment of acne vulgaris.

2 DOSAGE AND ADMINISTRATION

For topical use only. Not for oral, ophthalmic, or intravaginal use.

After the skin is gently washed and patted dry, apply approximately a pea-sized amount of ACZONE Gel, 5%, in a thin layer to the acne affected areas twice daily. Rub in ACZONE Gel, 5%, gently and completely. ACZONE Gel, 5%, is gritty with visible drug substance particles. Wash hands after application of ACZONE Gel, 5%.

If there is no improvement after 12 weeks, treatment with ACZONE Gel, 5%, should be reassessed.

3 DOSAGE FORMS AND STRENGTHS

Gel, 5%. Each gram of ACZONE gel contains 50 mg of dapsone in a white to pale yellow gel.

4 CONTRAINDICATIONS

None.

5 WARNINGS AND PRECAUTIONS

5.1 Methemoglobinemia

Cases of methemoglobinemia, with resultant hospitalization, have been reported postmarketing in association with ACZONE Gel, 5% treatment. Patients with glucose‐6‐phosphate dehydrogenase deficiency or congenital or idiopathic methemoglobinemia are more susceptible to drug‐induced methemoglobinemia. Avoid use of ACZONE Gel, 5% in those patients with congenital or idiopathic methemoglobinemia.

Signs and symptoms of methemoglobinemia may be delayed some hours after exposure. Initial signs and symptoms of methemoglobinemia are characterized by a slate grey cyanosis seen in, e.g., buccal mucous membranes, lips and nail beds. Advise patients to discontinue ACZONE Gel, 5% and seek immediate medical attention in the event of cyanosis.

Dapsone can cause elevated methemoglobin levels particularly in conjunction with methemoglobin‐inducing agents.

5.2 Hematologic Effects

Oral dapsone treatment has produced dose-related hemolysis and hemolytic anemia. Individuals with glucose-6-phosphate dehydrogenase (G6PD) deficiency are more prone to hemolysis with the use of certain drugs. G6PD deficiency is most prevalent in populations of African, South Asian, Middle Eastern, and Mediterranean ancestry.

Some subjects with G6PD deficiency using ACZONE Gel developed laboratory changes suggestive of hemolysis. There was no evidence of clinically relevant hemolysis or anemia in patients treated with ACZONE Gel, 5%, including patients who were G6PD deficient.

Discontinue ACZONE Gel, 5%, if signs and symptoms suggestive of hemolytic anemia occur. Avoid use of ACZONE Gel, 5% in patients who are taking oral dapsone or antimalarial medications because of the potential for hemolytic reactions. Combination of ACZONE Gel, 5%, with trimethoprim/sulfamethoxazole (TMP/SMX) may increase the likelihood of hemolysis in patients with G6PD deficiency.

5.3 Peripheral Neuropathy

Peripheral neuropathy (motor loss and muscle weakness) has been reported with oral dapsone treatment. No events of peripheral neuropathy were observed in clinical trials with topical ACZONE Gel, 5% treatment.

5.4 Skin

Skin reactions (toxic epidermal necrolysis, erythema multiforme, morbilliform and scarlatiniform reactions, bullous and exfoliative dermatitis, erythema nodosum, and urticaria) have been reported with oral dapsone treatment. These types of skin reactions were not observed in clinical trials with topical ACZONE Gel, 5% treatment.

6 ADVERSE REACTIONS

6.1 Clinical Studies Experience

Because clinical trials are conducted under widely varying conditions, adverse reaction rates observed in the clinical trials of a drug cannot be directly compared to rates in the clinical trials of another drug and may not reflect the rates observed in practice.

Serious adverse reactions reported in subjects treated with ACZONE Gel, 5%, during clinical trials included but were not limited to the following:

- Nervous system/Psychiatric – Suicide attempt, tonic clonic movements.
- Gastrointestinal – Abdominal pain, severe vomiting, pancreatitis.
- Other – Severe pharyngitis

In the clinical trials, a total of 12 out of 4032 subjects were reported to have depression (3 of 1660 treated with vehicle and 9 of 2372 treated with ACZONE Gel, 5%). Psychosis was reported in 2 of 2372 subjects treated with ACZONE Gel, 5%, and in 0 of 1660 subjects treated with vehicle.

Combined contact sensitization/irritation studies with ACZONE Gel, 5%, in 253 healthy subjects resulted in at least 3 subjects with moderate erythema. ACZONE Gel, 5%, did not induce phototoxicity or photoallergy in human dermal safety studies.

ACZONE Gel, 5%, was evaluated for 12 weeks in four controlled trials for local cutaneous events in 1819 subjects. The most common events reported from these studies include oiliness/peeling, dryness, and erythema. These data are shown by severity in Table 1 below.

Table 1 – Application Site Adverse Reactions by Maximum Severity
 | ACZONE® (N=1819) |  |  | Vehicle (N=1660)
Application Site Event | Mild | Moderate | Severe | Mild | Moderate | Severe
Erythema | 9% | 5% | <1% | 9% | 6% | <1%
Dryness | 14% | 3% | <1% | 14% | 4% | <1%
Oiliness/Peeling | 13% | 6% | <1% | 15% | 6% | <1%

The adverse reactions occurring in at least 1% of subjects in either arm in the four vehicle controlled trials are presented in Table 2.

Table 2 – Adverse Reactions Occurring in at Least 1% of Subjects
 | ACZONE® N=1819 | Vehicle N=1660
Application Site Reaction NOS | 18% | 20%
Application Site Dryness | 16% | 17%
Application Site Erythema | 13% | 14%
Application Site Burning | 1% | 2%
Application Site Pruritus | 1% | 1%
Pyrexia | 1% | 1%
Nasopharyngitis | 5% | 6%
Upper Respiratory Tract Inf. NOS | 3% | 3%
Sinusitis NOS | 2% | 1%
Influenza | 1% | 1%
Pharyngitis | 2% | 2%
Cough | 2% | 2%
Joint Sprain | 1% | 1%
Headache NOS | 4% | 4%

NOS = Not otherwise specified

One subjects treated with ACZONE Gel in the clinical trials had facial swelling which led to discontinuation of medication.

In addition, 486 subjects were evaluated in a 12 month safety trial. The adverse event profile in this trial was consistent with that observed in the vehicle-controlled trials.

6.2 Experience with Oral Use of Dapsone

Although not observed in the clinical trials with ACZONE Gel (topical dapsone) serious adverse reactions have been reported with oral use of dapsone, including agranulocytosis, hemolytic anemia, peripheral neuropathy (motor loss and muscle weakness), and skin reactions (toxic epidermal necrolysis, erythema multiforme, morbilliform and scarlatiniform reactions, bullous and exfoliative dermatitis, erythema nodosum, and urticaria).

6.3 Postmarketing Experience

Because these reactions are reported voluntarily from a population of uncertain size, it is not always possible to reliably estimate their frequency or establish a causal relationship to drug exposure.

The following adverse reactions have been identified during post-approval use of topical dapsone:

methemoglobinemia, rash (including erythematous rash, application site rash) and swelling of face (including lip swelling, eye swelling)

7 DRUG INTERACTIONS

7.1 Trimethoprim-Sulfamethoxazole

A drug-drug interaction study evaluated the effect of the use of ACZONE Gel, 5%, in combination with double strength (160 mg/800 mg) trimethoprim-sulfamethoxazole (TMP/SMX). During co-administration, systemic levels of TMP and SMX were essentially unchanged. However, levels of dapsone and its metabolites increased in the presence of TMP/SMX. Systemic exposure (AUC0-12) of dapsone and N-acetyl-dapsone (NAD) were increased by about 40% and 20% respectively in the presence of TMP/SMX. Notably, systemic exposure (AUC0-12) of dapsone hydroxylamine (DHA) was more than doubled in the presence of TMP/SMX. Exposure from the proposed topical dose is about 1% of that from the 100 mg oral dose, even when co-administered with TMP/SMX.

7.2 Topical Benzoyl Peroxide

Topical application of ACZONE Gel followed by benzoyl peroxide in subjects with acne vulgaris resulted in a temporary local yellow or orange discoloration of the skin and facial hair (reported by 7 out of 95 subjects in a clinical study) with resolution in 4 to 57 days.

7.3 Drug Interactions with Oral Dapsone

Certain concomitant medications (such as rifampin, anticonvulsants, St. John’s wort) may increase the formation of dapsone hydroxylamine, a metabolite of dapsone associated with hemolysis. With oral dapsone treatment, folic acid antagonists such as pyrimethamine have been noted to possibly increase the likelihood of hematologic reactions.

7.4 Concomitant Use with Drugs that Induce Methemoglobinemia

Concomitant use of ACZONE with drugs that induce methemoglobinemia such as sulfonamides, acetaminophen, acetanilide, aniline dyes, benzocaine, chloroquine, dapsone, naphthalene, nitrates and nitrites, nitrofurantoin, nitroglycerin, nitroprusside, pamaquine, para‐aminosalicylic acid, phenacetin, phenobarbital, phenytoin, primaquine, and quinine may increase the risk for developing methemoglobinemia [see Warnings and Precautions (5.1)].

8 USE IN SPECIFIC POPULATIONS

8.1 Pregnancy

Risk Summary
There are no available data on ACZONE Gel, 5%, use in pregnant women to inform a drug-associated risk for adverse developmental outcomes. In animal reproduction studies, oral doses of dapsone administered to pregnant rats and rabbits during organogenesis that resulted in systemic exposures more than 250 times the systemic exposure at the maximum recommended human dose (MRHD) of ACZONE Gel, 5%, resulted in embryocidal effects. When orally administered to rats from the onset of organogenesis through the end of lactation at systemic exposures approximately 400 times the exposure at the MRHD, dapsone resulted in increased stillbirths and decreased pup weight [see Data].

The estimated background risks of major birth defects and miscarriage for the indicated population are unknown. In the U.S. general population, the estimated background risk of major birth defects and miscarriage in clinically recognized pregnancies is 2-4% and 15-20%, respectively.

Data
Animal Data
Dapsone has been shown to have an embryocidal effect in rats and rabbits when administered orally daily to females during organogenesis at dosages of 75 mg/kg/day and 150 mg/kg/day, respectively. These dosages resulted in systemic exposures that represented approximately 956 times [rats] and 289 times [rabbits] the systemic exposure observed in human females as a result of use of the MRHD of ACZONE Gel, 5%, based on AUC comparisons. These effects were probably secondary to maternal toxicity.

Dapsone was assessed for effects on perinatal/postnatal pup development and postnatal maternal behavior and function in a study in which dapsone was orally administered to female rats daily beginning on the seventh day of gestation and continuing until the twenty-seventh day postpartum. Maternal toxicity (decreased body weight and food consumption) and developmental effects (increase in stillborn pups and decreased pup weight) were seen at a dapsone dose of 30 mg/kg/day (approximately 382 times the systemic exposure that is associated with the MRHD of ACZONE Gel, 5%, based on AUC comparisons). No effects were observed on the viability, physical development, behavior, learning ability, or reproductive function of surviving pups.

8.2 Lactation

Risk Summary
There is no information regarding the presence of topical dapsone in breastmilk, the effects on the breastfed infant, or the effects on milk production. Orally administered dapsone appears in human milk and could result in hemolytic anemia and hyperbilirubinemia especially in infants with G6PD deficiency. Systemic absorption of dapsone following topical application is minimal relative to oral dapsone administration; however, it is known that dapsone is present in human milk following administration of oral dapsone.

8.4 Pediatric Use

Safety and efficacy was evaluated in 1169 children aged 12-17 years old treated with ACZONE Gel, 5%, in the clinical trials. The adverse event rate for ACZONE Gel, 5%, was similar to the vehicle control group. Safety and efficacy was not studied in pediatric patients less than 12 years of age, therefore ACZONE Gel, 5%, is not recommended for use in this age group.

8.5 Geriatric Use

Clinical trials of ACZONE Gel, 5%, did not include sufficient number of subjects aged 65 and over to determine whether they respond differently from younger subjects.

8.6 G6PD Deficiency

ACZONE Gel, 5% and vehicle were evaluated in a randomized, double-blind, cross-over design clinical trial of 64 subjects with G6PD deficiency and acne vulgaris. Subjects were Black (88%), Asian (6%), Hispanic (2%) or of other racial origin (5%). Blood samples were taken at Baseline, Week 2, and Week 12 during both vehicle and ACZONE Gel, 5% treatment periods. There were 56 out of 64 subjects who had a Week 2 blood draw and applied at least 50% of treatment applications. Table 3 contains results from testing of relevant hematology parameters for these two treatment periods. ACZONE Gel was associated with a 0.32 g/dL drop in hemoglobin after two weeks of treatment, but hemoglobin levels generally returned to baseline levels at Week 12.

Table 3 – Mean Hemoglobin, Bilirubin, and Reticulocyte Levels in Acne Subjects with G6PD Deficiency in ACZONE/Vehicle Cross-Over Study
 |  | ACZONE® |  | Vehicle
 |  | N | Mean | N | Mean
Hemoglobin (g/dL) | Pre-treatment | 53 | 13.44 | 56 | 13.36
 | 2 weeks | 53 | 13.12 | 55 | 13.34
 | 12 weeks | 50 | 13.42 | 50 | 13.37
Bilirubin (mg/dL) | Pre-treatment | 54 | 0.58 | 56 | 0.55
 | 2 weeks | 53 | 0.65 | 55 | 0.56
 | 12 weeks | 50 | 0.61 | 50 | 0.62
Reticulocytes (%) | Pre-treatment | 53 | 1.30 | 55 | 1.34
 | 2 weeks | 53 | 1.51 | 55 | 1.34
 | 12 weeks | 50 | 1.48 | 50 | 1.41

There were no changes from baseline in haptoglobin or lactate dehydrogenase during ACZONE or vehicle treatment at either the 2-week or 12-week time point.

The proportion of subjects who experienced decreases in hemoglobin ≥1 g/dL was similar between ACZONE Gel, 5% and vehicle treatment (8 of 58 subjects had such decreases during ACZONE treatment compared to 7 of 56 subjects during vehicle treatment among subjects with at least one on-treatment hemoglobin assessment). Subgroups based on gender, race, or G6PD enzyme activity did not display any differences in laboratory results from the overall study group. There was no evidence of clinically significant hemolytic anemia in this study. Some of these subjects developed laboratory changes suggestive of hemolysis.

11 DESCRIPTION

ACZONE Gel, 5%, contains dapsone, a sulfone, in an aqueous gel base for topical dermatologic use. ACZONE Gel, 5% is a gritty translucent material with visible drug substance particles. Chemically, dapsone has an empirical formula of C12H12N2O2S. It is a white, odorless crystalline powder that has a molecular weight of 248. Dapsone’s chemical name is 4,4’-diaminodiphenylsulfone and its structural formula is:

Each gram of ACZONE Gel, 5%, contains 50 mg of dapsone, USP, in a gel of carbomer homopolymer type C; diethylene glycol monoethyl ether, NF; methylparaben, NF; sodium hydroxide, NF; and purified water, USP.

12 CLINICAL PHARMACOLOGY

12.1 Mechanism of Action

The mechanism of action of dapsone gel in treating acne vulgaris is not known.

12.3 Pharmacokinetics

An open-label study compared the pharmacokinetics of dapsone after ACZONE Gel, 5%, (110 ± 60 mg/day) was applied twice daily (~BSA 22.5%) for 14 days (n=18) with a single 100 mg dose of oral dapsone administered to a subgroup of patients (n=10) in a crossover design. On Day 14 the mean dapsone AUC0-24h was 415 ± 224 ng•h/mL for ACZONE Gel, 5%, whereas following a single 100 mg dose of oral dapsone the AUC0-infinity was 52,641 ± 36,223 ng•h/mL. Exposure after the oral dose of 100 mg dapsone was approximately 100 times greater than after the topical ACZONE Gel, 5% dose, twice a day.

In a long-term safety study of ACZONE Gel, 5% treatment, periodic blood samples were collected up to 12 months to determine systemic exposure of dapsone and its metabolites in approximately 500 patients. Based on the measurable dapsone concentrations from 408 patients (M=192, F=216), obtained at month 3, neither gender, nor race appeared to affect the pharmacokinetics of dapsone. Similarly, dapsone exposures were approximately the same between the age groups of 12-15 years (N=155) and those greater than or equal to 16 years (N=253). There was no evidence of increasing systemic exposure to dapsone over the study year in these patients.

12.4 Microbiology

In Vivo Activity: No microbiology or immunology studies were conducted during dapsone gel clinical trials.

Drug Resistance: No dapsone resistance studies were conducted during dapsone gel clinical trials. Because no microbiology studies were done, there are no data available as to whether dapsone treatment may have resulted in decreased susceptibility of Propionibacterium acnes, an organism associated with acne, to other antimicrobials that may be used to treat acne. Therapeutic resistance to dapsone has been reported for Mycobacterium leprae, when patients have been treated with oral dapsone.

13 NONCLINICAL TOXICOLOGY

13.1 Carcinogenesis, Mutagenesis, Impairment of Fertility

Dapsone was not carcinogenic to rats when orally administered to females for 92 weeks or males for 100 weeks at dose levels up to 15 mg/kg/day (approximately 231 times the systemic exposure observed in humans as a result of use of the MRHD of ACZONE Gel, 5%, based on AUC comparisons).

No evidence of potential to induce carcinogenesis was observed in a dermal study in which dapsone gel was topically applied to Tg.AC transgenic mice for approximately 26 weeks. Dapsone concentrations of 3%, 5%, and 10% were evaluated; 3% material was judged to be the maximum tolerated dosage.

Dapsone was negative in a bacterial reverse mutation assay (Ames test), and was negative in a micronucleus assay conducted in mice. Dapsone was positive (clastogenic) in a chromosome aberration assay conducted with Chinese hamster ovary (CHO) cells.

The effects of dapsone on fertility and general reproductive performance were assessed in male and female rats following oral dosing. Dapsone reduced sperm motility at dosages of 3 mg/kg/day or greater (approximately 15 times the systemic exposure that is associated with the MRHD of ACZONE Gel, 5%, based on AUC comparisons) when administered daily beginning 63 days prior to mating and continuing through the mating period. The mean numbers of embryo implantations and viable embryos were significantly reduced in untreated females mated with males that had been dosed at 12 mg/kg/day or greater (approximately 127 times the systemic exposure that is associated with the MRHD of ACZONE Gel, 5%, based on AUC comparisons), presumably due to reduced numbers or effectiveness of sperm, indicating impairment of fertility. When administered to female rats at a dosage of 75 mg/kg/day (approximately 956 times the systemic exposure that is associated with the MRHD of ACZONE Gel, 5%, based on AUC comparisons) for 15 days prior to mating and for 17 days thereafter, dapsone reduced the mean number of implantations, increased the mean early resorption rate, and reduced the mean litter size. These effects probably were secondary to maternal toxicity.

14 CLINICAL STUDIES

Two randomized, double-blind, vehicle-controlled, clinical trials were conducted to evaluate ACZONE Gel, 5%, for the treatment of subjects with acne vulgaris (N=1475 and 1525). The trials were designed to enroll subjects 12 years of age and older with 20 to 50 inflammatory and 20 to 100 non-inflammatory lesions at baseline. In these trials, subjects applied either ACZONE Gel, 5%, or vehicle control twice daily for up to 12 weeks. Efficacy was evaluated in terms of success on the Global Acne Assessment Score (no or minimal acne) and in the percent reduction in inflammatory, non-inflammatory, and total lesions.

The Global Acne Assessment Score was a 5-point scale as follows:

0 None: no evidence of facial acne vulgaris
1 Minimal: few non-inflammatory lesions (comedones) are present; a few inflammatory lesions (papules/pustules) may be present
2 Mild: several to many non-inflammatory lesions (comedones) are present; a few inflammatory lesions (papules/pustules) are present
3 Moderate: many non-inflammatory (comedones) and inflammatory lesions (papules/pustules) are present; no nodulo-cystic lesions are allowed
4 Severe: significant degree of inflammatory disease; papules/pustules are a predominant feature; a few nodulo-cystic lesions may be present; comedones may be present.

The success rates on the Global Acne Assessment Score (no or minimal acne) at Week 12 are presented in Table 4.

Table 4 - Success (No or Minimal Acne) on the Global Acne Assessment Score at Week 12
 | Study 1* |  | Study 2*
 | ACZONE N=699 | Vehicle N=687 | ACZONE N=729 | Vehicle N=738
Subjects with No or Minimal Acne | 291 (42%) | 223 (32%) | 253 (35%) | 206 (28%)

*Analysis excludes subjects classified with minimal acne at baseline

Table 5 presents the mean percent reduction in inflammatory, non-inflammatory, and total lesions from baseline to Week 12.

Table 5 - Percent Reduction in Lesions from Baseline to Week 12
 | Study 1 |  | Study 2
 | ACZONE N=745 | Vehicle N=740 | ACZONE N=761 | Vehicle N=764
Inflammatory | 46% | 42% | 48% | 40%
Non-Inflammatory | 31% | 24% | 30% | 21%
Total | 38% | 32% | 37% | 29%

The clinical trials enrolled about equal proportions of male and female subjects. Female subjects tended to have greater percent reductions in lesions and greater success on the Global Acne Assessment Score than males. The breakdown by race in the clinical trials was about 73% Caucasian, 14% Black, 9% Hispanic, and 2% Asian. Efficacy results were similar across the racial subgroups.

16 HOW SUPPLIED/STORAGE AND HANDLING

ACZONE (dapsone) Gel, 5%, is supplied in the following size tubes:

NDC 16110-367-60
60 gram laminate tube

NDC 16110-367-90
90 gram laminate tube

Store ACZONE gel at controlled room temperature, 20°-25°C (68°-77°F), excursions permitted to 15°-30ºC (59°-86ºF). Protect from freezing.

17 PATIENT COUNSELING INFORMATION

Advise the patient to read the FDA-approved patient labeling (Patient Information).

Hematological Effects

- Inform patients that methemoglobinemia can occur with topical dapsone treatment. Advise patients to seek immediate medical attention if they develop cyanosis [see Warnings and Precautions (5.1)].
- Inform patients who have G6PD deficiency that hemolytic anemia may occur with topical dapsone treatment. Advise patients to seek medical attention if they develop signs and symptoms suggestive of hemolytic anemia [see Warnings and Precautions (5.2)].

Important Administration Instructions

- Advise patients to apply ACZONE Gel, 5%, twice daily to the acne affected area [see Dosage and Administration (2)].
- ACZONE Gel, 5% is for topical use only.
- Do not apply ACZONE Gel, 5% to eyes, mouth, or mucous membranes.

Product of Italy
Distributed by Alrmirall, LLC, Exton, PA 19341, USAACZONE® is a trademark of Almirall, LLC.
Almirall® and its design are trademarks of Almirall, Inc.
©2019 Almirall, LLC. All rights reserved.

v1.0USPI3670

-------Cut Here ---------------------------------------------------------------------------------------------------------------

PATIENT INFORMATION
ACZONE® (AK-zōn) (dapsone) Gel, 5%

Important: For use on skin only (topical use). Do not use ACZONE® Gel, 5% in or on your mouth, eyes, or vagina.

What is ACZONE® Gel, 5%?
ACZONE® Gel, 5% is a prescription medicine used on your skin (topical) to treat acne vulgaris.
ACZONE® Gel has not been studied in children under 12 years of age.

Before using ACZONE® Gel, 5%, tell your doctor about all of your medical conditions, including if you:

- Have glucose-6-phosphate dehydrogenase deficiency (G6PD)
- Have higher than normal levels of methemoglobin in your blood (methemoglobinemia)
- Are pregnant or plan to become pregnant. It is not known if ACZONE® Gel, 5 % will harm your unborn baby.
- Are breastfeeding or plan to breastfeed. ACZONE® Gel, 5% can pass into your breast milk and may harm your baby. You and your doctor should decide if you will use ACZONE® Gel, 5% or breastfeed. You should not do both.

Tell your doctor about all the medicines you take, including prescription and over-the-counter medicines, vitamins, and herbal supplements. Especially tell your doctor if you are using acne medicines that contain benzoyl peroxide. Use of benzoyl peroxide with ACZONE® Gel, 5% at the same time may cause your skin or facial hair to temporarily turn yellow or orange at the site of application.

How should I use ACZONE® Gel, 5%?

- Use ACZONE® Gel, 5% exactly as your doctor tells you.
- Apply ACZONE® Gel, 5% twice a day.
- Gently wash and pat dry the areas of your skin where you will apply ACZONE® Gel, 5%.
- Apply a pea-sized amount of ACZONE® Gel, 5% in a thin layer to the areas of your skin that have acne.
- Rub ACZONE® Gel, 5% in gently and completely. It may feel gritty and you may see particles in the gel.
- Make sure to put the cap back on the ACZONE® Gel tube. Close it tightly.
- Wash your hands after applying ACZONE® Gel, 5%.
- If your acne does not get better after using ACZONE® Gel, 5% for 12 weeks, talk to your doctor about continuing treatment.

What are the possible side effects of ACZONE® Gel, 5%?
ACZONE® Gel, 5% may cause serious side effects, including:

- Decrease of oxygen in your blood caused by a certain type of abnormal red blood cell (methemoglobinemia). Stop using ACZONE® Gel, 5% and get medical help right away if your lips, nail beds, or the inside of your mouth turns grey or blue.
- Breakdown of red blood cells (hemolytic anemia). Some people with G6PD deficiency using ACZONE® Gel, 5% have developed mild hemolytic anemia. Stop using ACZONE® Gel, 5% and tell your doctor right away if you get any of the following signs and symptoms:

- back pain
- dark brown urine

- shortness of breath
- fever

- tiredness or weakness
- yellow or pale skin

The most common side effects of ACZONE® Gel, 5% include oiliness, peeling, dryness, and redness of the skin being treated.
These are not all of the possible side effects of ACZONE® Gel, 5%. Call your doctor for medical advice about side effects. You may report side effects to FDA at 1-800-FDA-1088.

How should I store ACZONE® Gel, 5%?

- Store ACZONE® Gel, 5% at room temperature 68ºF to 77ºF (20ºC to 25ºC).
- Protect ACZONE® Gel, 5% from freezing.

Keep ACZONE® Gel, 5% and all medicines out of the reach of children.

General information about the safe and effective use of ACZONE® Gel, 5%?
Medicines are sometimes prescribed for purposes other than those listed in a Patient Information leaflet. Do not use ACZONE® Gel, 5% for a condition for which it was not prescribed. Do not give ACZONE® Gel, 5% to other people, even if they have the same symptoms that you have. It may harm them. You can ask your pharmacist or doctor for information about ACZONE® Gel, 5% that is written for health professionals.

What are the ingredients in ACZONE® Gel, 5%?
Active ingredient: dapsone
Inactive ingredients: carbomer homopolymer type C, diethylene glycol monoethyl ether, methylparaben, sodium hydroxide, and purified water, USP.
Product of Italy
Distributed by Alrmirall, LLC, Exton, PA 19341, USAACZONE® is a trademark of Almirall, LLC.
Almirall® and its design are trademarks of Almirall, Inc.
©2019 Almirall, LLC. All rights reserved.
v1.0PPI3670
For more information, call 1-800-678-1605

This Patient Information has been approved by the U.S. Food and Drug Administration. Revised: 07/2019

PRINCIPAL DISPLAY PANEL

NDC 16110-367-60

Aczone®

(dapsone) gel, 5%

For tropical use only

60 g Rx only

almirall

PRINCIPAL DISPLAY PANEL

NDC 16110-367-90

Aczone®

(dapsone) gel, 5%

For tropical use only

^90 g Rx only

almirall